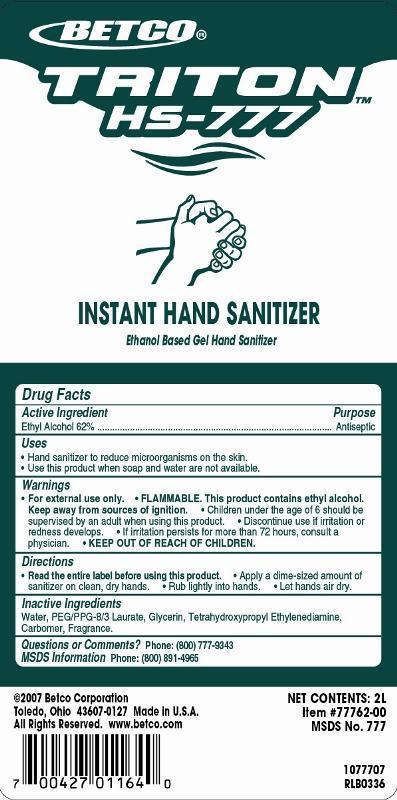 DRUG LABEL: Triton HS-777
NDC: 65601-777 | Form: SOAP
Manufacturer: Betco Corporation, Ltd.
Category: otc | Type: HUMAN OTC DRUG LABEL
Date: 20121112

ACTIVE INGREDIENTS: ALCOHOL 0.7 mL/1 mL
INACTIVE INGREDIENTS: WATER; GLYCERIN; POLYETHYLENE GLYCOL 400; EDETOL; CARBOMER HOMOPOLYMER TYPE C; D&C GREEN NO. 5

Triton HS-777

Triton HS-777

Active Ingredient

Ethyl Alcohol 62%

Triton HS-777

Uses

- Hand sanitizer to reduce microorganisms on the skin.
- Use in a variety of public settings when soap and water are not available.

Triton HS-777

Warnings

- For external use only.
- FLAMMABLE. This product contains ethyl alcohol. Keep away from sources of ignition.
- Children under the age of 6 should be supervised by an adult when using this product.
- Discontinue use is irritation or redness develops.
- KEEP OUT OF REACH OF CHILDREN.

Triton HS-777

Directions

- Read the entire label before using this product.
- Apply a dime-sized amount (1.5 mL) of sanitizer on clean, dry hands.
- Rub lightly into hands.
- Let hands air dry.

Triton HS-777

Inactive Ingredients

Water, Glycerin, PPG-3 Benzyl Ether Myristate, Tetrahydroxypropyl Ethelendiamine, Carbomer, Fragrance, D&C Green #5.

Triton HS-777

Questions or Comments? Phone: (800) 777-9343

MDS information:(800) 891-4965

Triton HS-777

Purpose

Antiseptic

Triton HS-777

KEEP OUT OF REACH OF CHILDREN

Triton HS-777

INSTANT HAND SANITIZER

Ethanol based Gel Hand Sanitizer

Net Contents: 2L

Item #77762-00

MSDS No. 777

2007 Betco Corporation

Toledo, Ohio 43607-0127 Made in U.S.A.

All Rights Reserved. www.betco.com